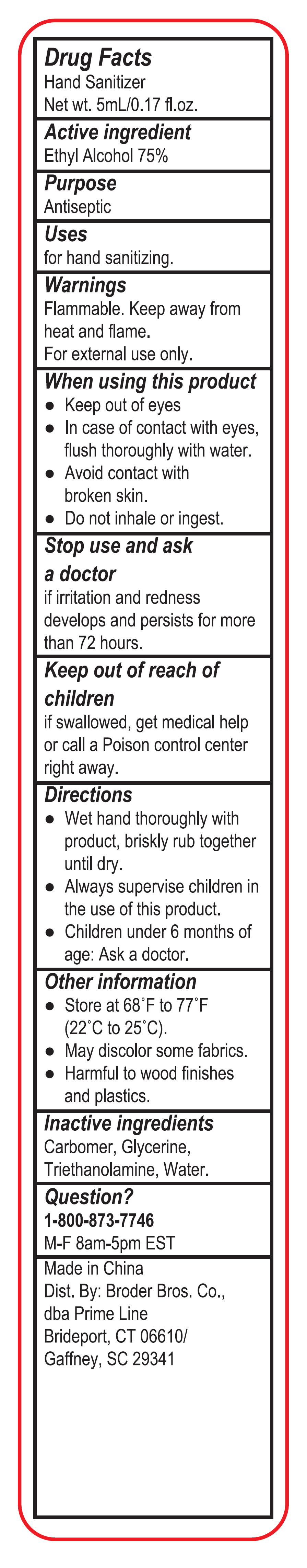 DRUG LABEL: Hand Sanitizer PP106
NDC: 80017-004 | Form: GEL
Manufacturer: Broder Bros Prime Line
Category: otc | Type: HUMAN OTC DRUG LABEL
Date: 20210306

ACTIVE INGREDIENTS: ALCOHOL 75 mL/100 mL
INACTIVE INGREDIENTS: CARBOMER HOMOPOLYMER, UNSPECIFIED TYPE; TROLAMINE; WATER; GLYCERIN

Hand Sanitizer PP106

Active ingredient

Alcohol 75% v/v. Purpose: Antiseptic

Purpose

Antiseptic, Hand Sanitizer

Uses

for hand sanitizing.

Warnings

Flammable, keep away from fire and flame

For external use only

When using this product

- Keep out of eyes
- In case of contact with eyes, flush thoroughly with water.
- Avoid contact with broken skin.
- Do not inhale or ingest.

Stop use and ask a doctor if irritation and redness develops and persists for more than 72 hours.

Keep our of reach of Children.

If swallowed, get medical help or call a Poison Control Center right away.

Directions

- Wet hands thoroughly with product, brisky rub together until dry.
- Always supervise children in the use of this product.
- Children under the age of 6 months: Ask a doctor.

Other information

- Store at 66 to 77 F (22 to 25 C)
- May discolor some fabrics
- Harmful to wood finishes and platics

Inactive ingredients

Carbomer, Glycerin, Triethanolamine, Water

Questions?

1-800-873-7746

M-F 8am-5pm EST

Package Label - Principal Display Panel

5 mL NDC: 80017-004-01

Hand Sanitizer PP106

Net wt. 5mL/0.17 fl.oz.